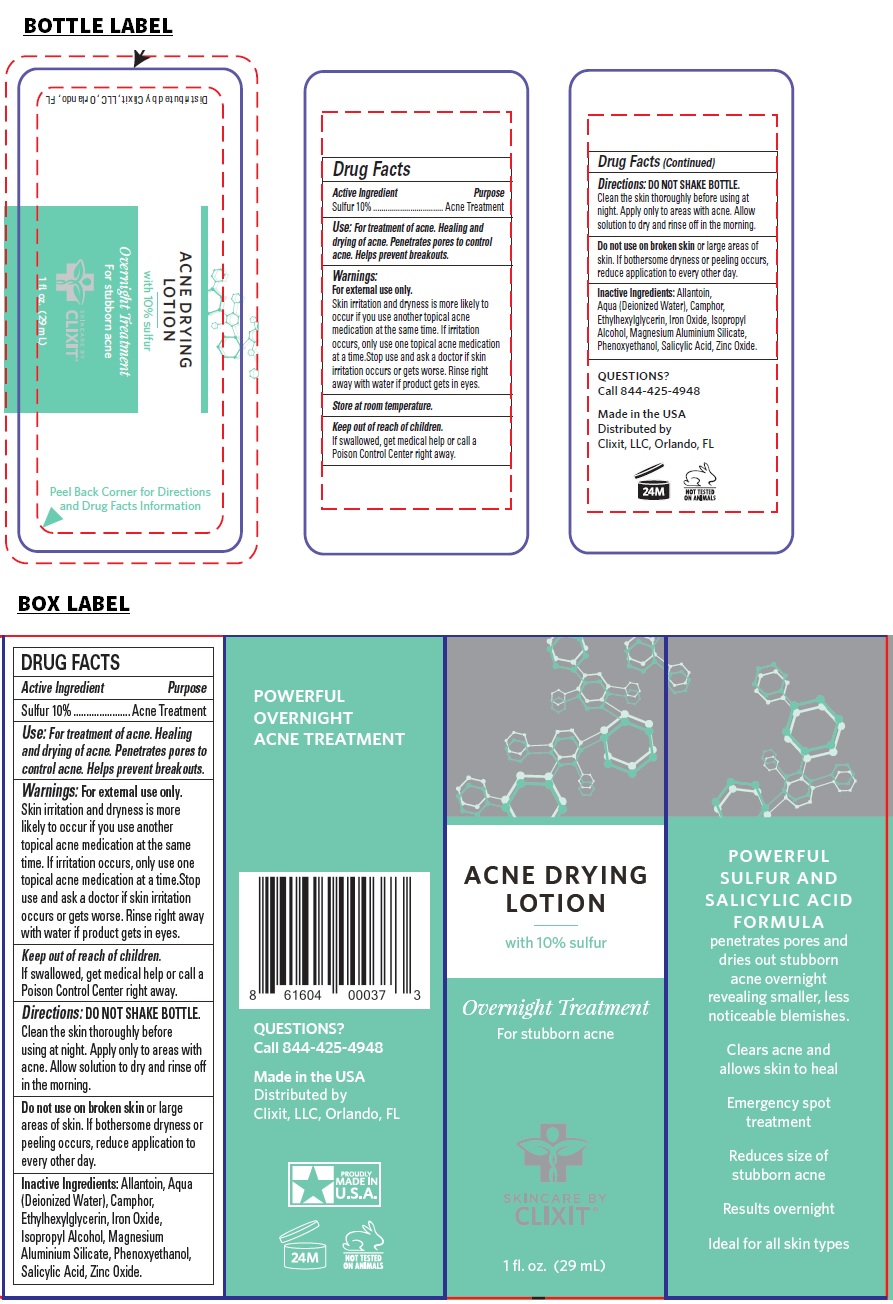 DRUG LABEL: CLIXIT ACNE DRYING
NDC: 71328-042 | Form: LOTION
Manufacturer: Clixit, Llc
Category: otc | Type: HUMAN OTC DRUG LABEL
Date: 20210416

ACTIVE INGREDIENTS: SULFUR 100 mg/1 mL
INACTIVE INGREDIENTS: ALLANTOIN; WATER; CAMPHOR (SYNTHETIC); ETHYLHEXYLGLYCERIN; FERRIC OXIDE RED; ISOPROPYL ALCOHOL; MAGNESIUM ALUMINUM SILICATE; PHENOXYETHANOL; SALICYLIC ACID; ZINC OXIDE

CLIXIT® ACNE DRYING LOTION

Active Ingredient

Sulfur 10%

Purpose

Acne Treatment

Use:

For treatment of acne. Healing and drying of acne. Penetrates pores to control acne. Helps prevent breakouts.

Warnings:

For external use only.
Skin irritation and dryness is more likely to occur if you use another topical acne medication at the same time. If irritation occurs, only use one topical acne medication at a time.Stop use and ask a doctor if skin irritation occurs or gets worse. Rinse right away with water if product gets in eyes.

Keep out of reach of children.
If swallowed, get medical help or call a Poison Control Center right away.

Directions:

DO NOT SHAKE BOTTLE.
Clean the skin thoroughly before using at night. Apply only to areas with acne. Allow solution to dry and rinse off in the morning.

Do not use on broken skin or large areas of skin. If bothersome dryness or peeling occurs, reduce application to every other day.

Inactive Ingredients:

Allantoin, Aqua (Deionized Water), Camphor, Ethylhexylglycerin, Iron Oxide, Isopropyl Alcohol, Magnesium Aluminium Silicate, Phenoxyethanol, Salicylic Acid, Zinc Oxide.

Overnight Treatment

For stubborn acne

SKINCARE BY CLIXIT®

POWERFUL SULFUR AND SALICYLIC ACID FORMULA penetrates pores and dries out stubborn acne overnight revealing smaller, less noticeable blemishes.

Clears acne and allows skin to heal

Emergency spot treatment

Reduces size of stubborn acne

Results overnight

Ideal for all skin types

POWERFUL OVERNIGHT ACNE TREATMENT

QUESTIONS?
Call 844-425-4948

Made in the USA

Distributed by
Clixit, LLC, Orlando, FL

NOT TESTED ON ANIMALS